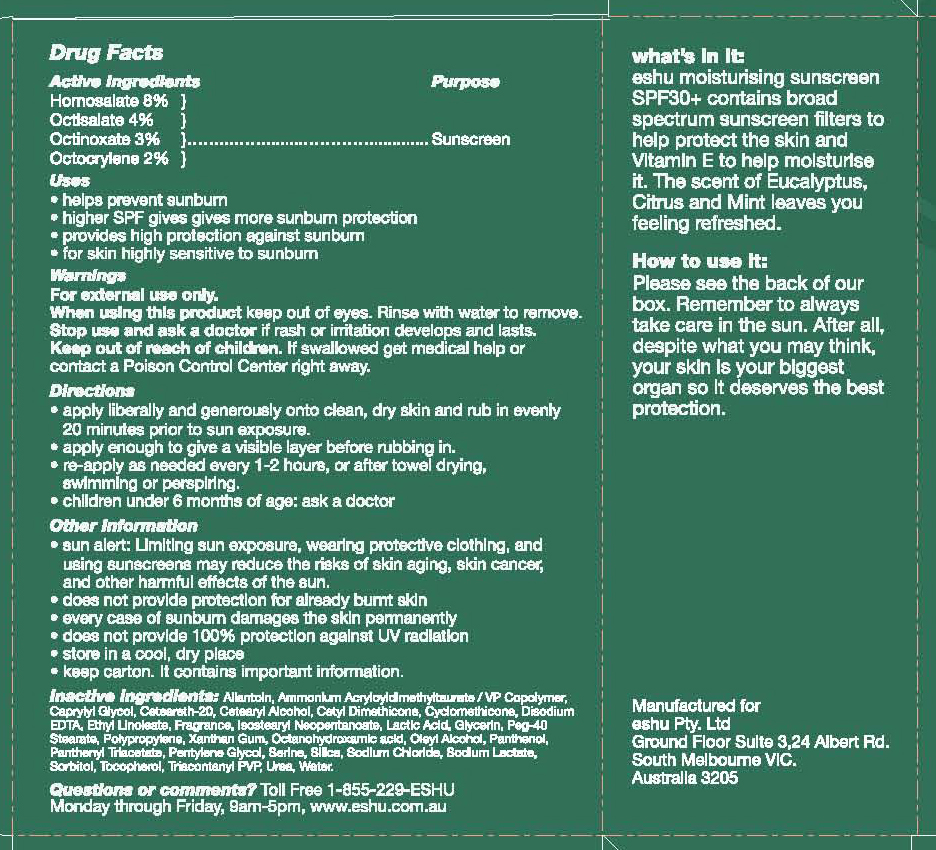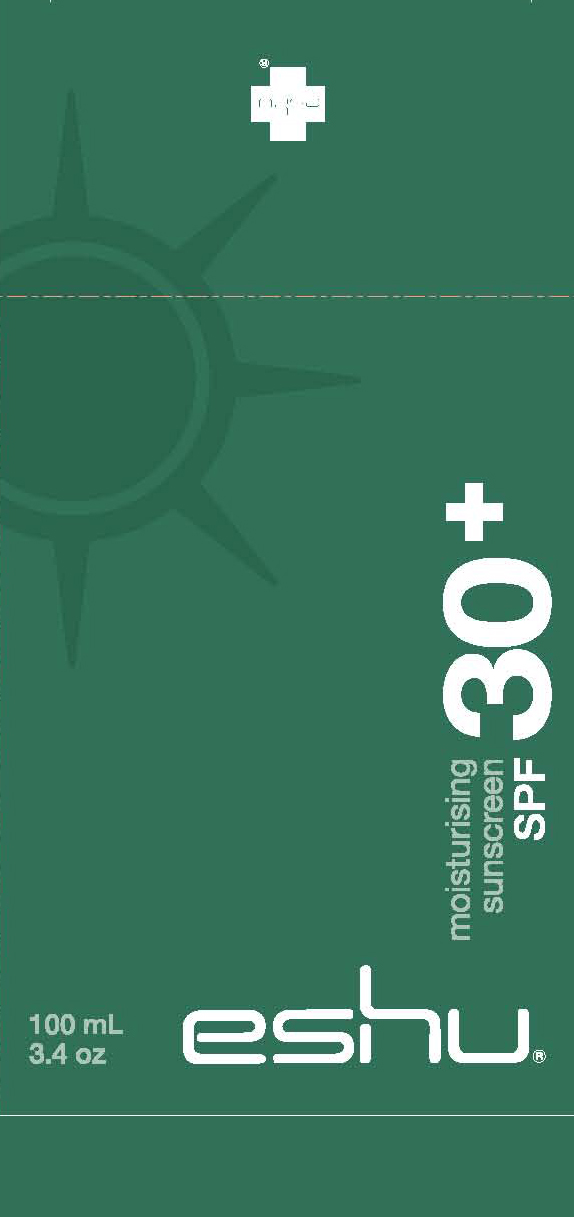 DRUG LABEL: moisturising sunscreen
NDC: 42315-672 | Form: CREAM
Manufacturer: Eshu Pty Ltd
Category: otc | Type: HUMAN OTC DRUG LABEL
Date: 20120105

ACTIVE INGREDIENTS: HOMOSALATE 8 mL/100 mL; OCTISALATE 4 mL/100 mL; OCTINOXATE 3 mL/100 mL
INACTIVE INGREDIENTS: ALLANTOIN; CAPRYLYL GLYCOL; CETOSTEARYL ALCOHOL; CYCLOMETHICONE; EDETATE DISODIUM; ETHYL LINOLEATE; LACTIC ACID; GLYCERIN; POLYOXYL 40 STEARATE; XANTHAN GUM; OLEYL ALCOHOL; PANTHENOL; PENTYLENE GLYCOL; SERINE; SILICON DIOXIDE; SODIUM CHLORIDE; SODIUM LACTATE; SORBITOL

Moisturizing Sunscreen SPF 30+

Active ingredients Purpose

Homosalate 8% Sunscreen

Octisalate 4% Sunscreen

Octinoxate 3% Sunscreen

Octocrylene 2% Sunscreen

Uses

-Helps prevent sunburn

-higher SPF gives more sunburn protection

-provides high protection against sunburn

-for skin highly sensitive to sunburn

Keep out of reach of children

-Stop use and ask a doctor if rash or irritation occurs.
-Sun Alert: Limiting sun exposure, wearing protective clothing, and using sunscreen may reduce risk of skin aging, skin cancer, and other harmful effects of the sun
-Does not provide protection for already burnt skin
-every case of sunburn damages the skin permanently
-does not provide 100% protection against UV radiation
-store in a cool dry place
-keep carton. It contains important information

warnings

For external use only

When using this product keep out of eyes. rinse with water to remove

If swallowed, get medical help or call a poison control center right away

Directions
-apply liberally and generously onto clean, dry skin and rub in evenly 20 minutes prior to sun exposure
-apply enough to give a visible layer before rubbing in .
-re-apply as needed every 1-2 hours, or after towel drying, swimming, or perspiring.
-Children under 6 years of age: ask a doctor.

Inactive ingredients

Allantoin, Ammonium Acryloyldimethicone/VP copolymer, Caprylyl Glycol, Ceteareth-20, Cetearyl Alcohol, Cetyl Dimethicone, Cylcomethicone, Disodium EDTA, Ethyl Linoleate, Fragrance, Isostearyl Neopentoate, Lactic Acid, Glycerin, Peg-40 Stearate, Polypropylene, Xanthan gum, Octanohydroxamic acid, Oleyl Alcohol, Panthenol, Panthenyl Triacetate, Pentylene Glycol, Serine, Silica, Sodium chloride, Sodium Lactate, Sorbitol, Tocopherol, Triacontanyl PVP, Urea, water.

PACKAGE LABEL

Moisturizing Sunscreen SPF 30+

100 mL/3.4 oz